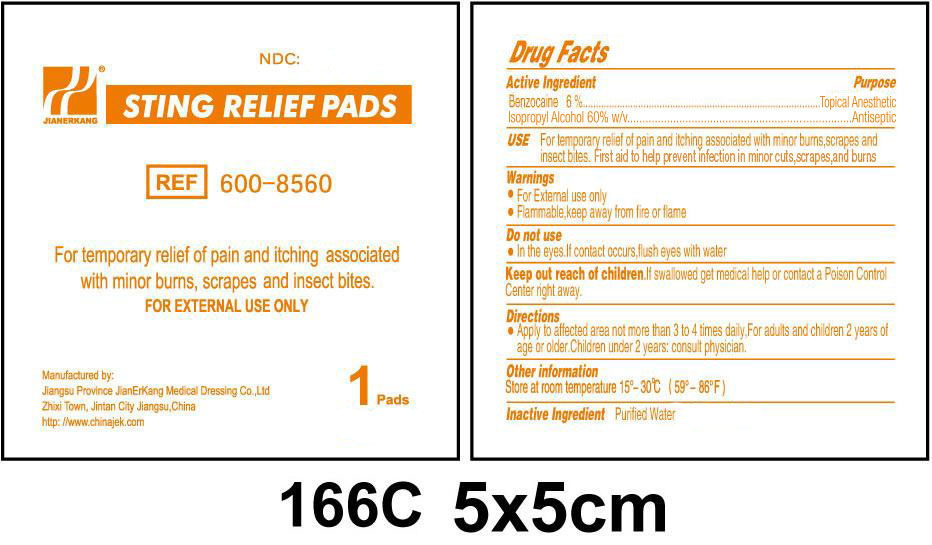 DRUG LABEL: Sting Relief
NDC: 34645-4190 | Form: SWAB
Manufacturer: Jianerkang Medical Co., Ltd
Category: otc | Type: HUMAN OTC DRUG LABEL
Date: 20231023

ACTIVE INGREDIENTS: BENZOCAINE 6 g/100 g; ISOPROPYL ALCOHOL 60 g/100 g
INACTIVE INGREDIENTS: WATER

Sting Relief Pads

Active Ingredient

Benzocaine 6%

Isopropyl Alcohol 60% w/v

Purpose

Topical Anesthetic

Antiseptic

USE

For temporary relief of pain and itching associated with minor burns, scrapes and insect bites. First aid to help prevent infection in minor cuts, scrapes, and burns

Warnings

- For External use only
- Flammable, keep away from fire or flame

Do not use

- In the eyes. If contact occurs, flush eyes with water

Keep out of reach of children.

If swallowed get medical help or contact a Poison Control Center right away.

Directions

- Apply to affected area not more than 3 to 4 times daily. For adults and children 2 years of age or older. Children under 2 years: consult physician.

Other information

Store at room temperature 15° - 30°C (59° - 86°F)

Inactive Ingredient

Purified Water